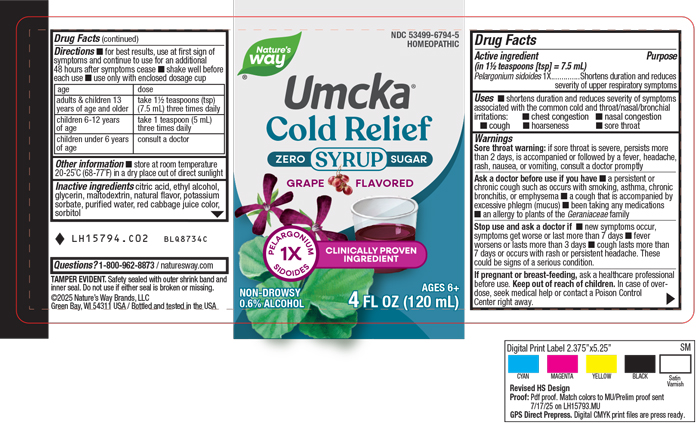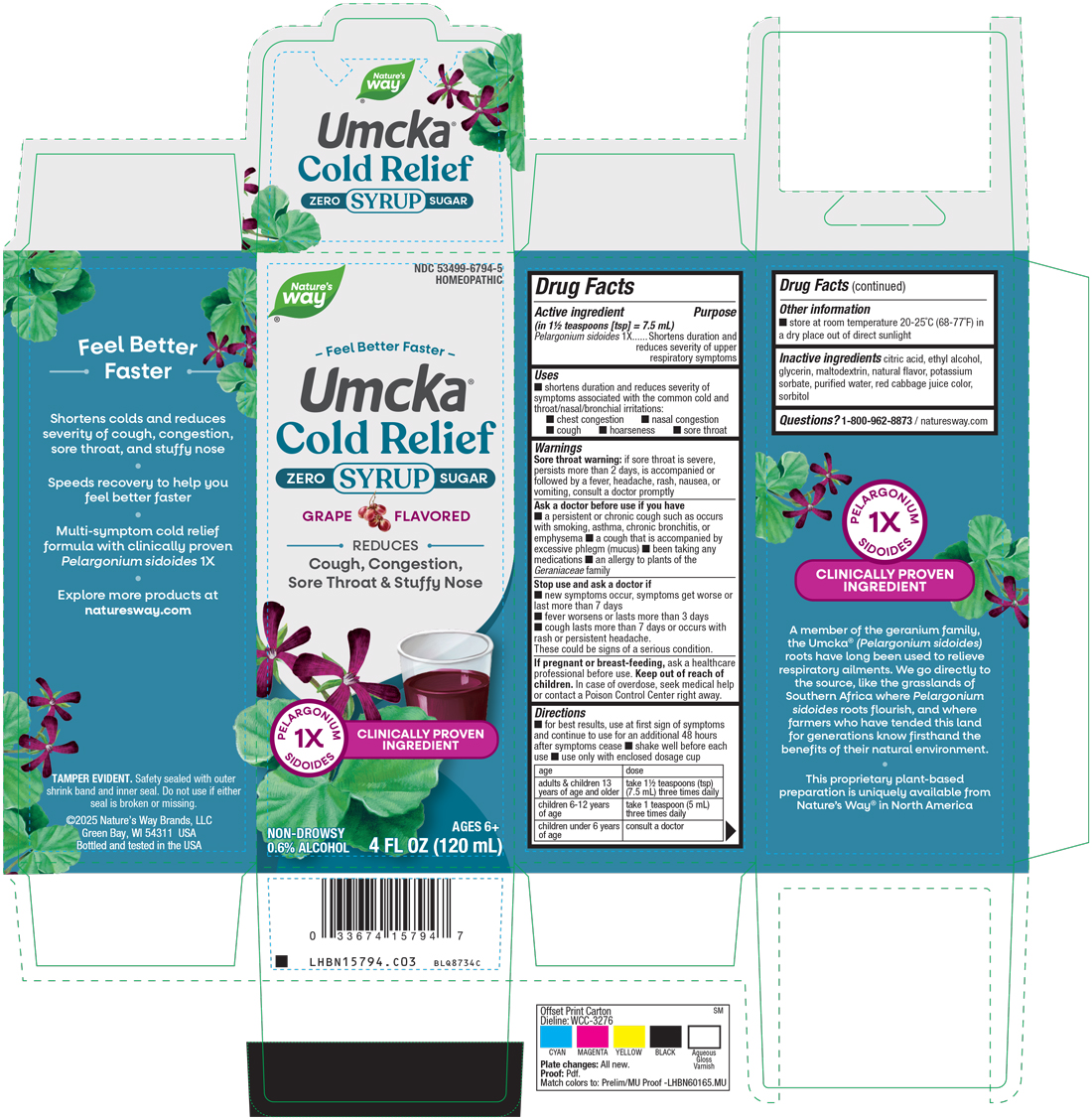 DRUG LABEL: Cold Relief Zero Sugar Grape
NDC: 53499-6794 | Form: SYRUP
Manufacturer: Schwabe North America, Inc
Category: homeopathic | Type: HUMAN OTC DRUG LABEL
Date: 20250916

ACTIVE INGREDIENTS: PELARGONIUM SIDOIDES ROOT 1 [hp_X]/120 mL
INACTIVE INGREDIENTS: ANHYDROUS CITRIC ACID; ALCOHOL; MALTODEXTRIN; WATER; CABBAGE; SORBITOL; GLYCERIN; POTASSIUM SORBATE

Cold Relief Zero Sugar Grape Syrup

Active Ingredient

Pelargonium sidoides 1X

Inactive Ingredients

Citric Acid

Ethyl Alcohol

Glycerin

Maltodextrin

Natural Flavor

Potassium Sorbate

Purified Water

Red Cabbage Juice Color

Sorbitol

Dosage and Administration

Directions

For best results, use at first sign of symptoms and continue to use for an additional 48 hours after symptoms cease.

Shake well before each use.

Use only with enclosed dosage cup.

Adults & children 13 years of age and older: Take 1 ½ teaspoon (tsp) (7.5 mL) three times daily.

Children 6-12 years of age: Take 1 teaspoon (5mL) three times daily.

Children under 6 years of age: Consult a doctor.

Indications & Usage

Shortens duration and reduces severity of symptoms associated with the common cold and throat/nasal/bronchial irritations: chest congestion, nasal congestion, cough, hoarseness, sore throat.

Purpose

Shortens duration and reduces severity of symptoms associated with the common cold and throat/nasal/bronchial irritations: chest congestion, nasal congestion, cough, hoarseness, sore throat.

Warnings

Sore throat warning: If sore throat is severe, persists more than 2 days, is accompanied or followed by a fever, headache, rash, nausea, or vomiting, consult a doctor promptly.

Ask Doctor

Ask a doctor before use if you have a persistent or chronic cough such as occurs with smoking, asthma, chronic bronchitis or emphysema, a cough that is accompanied by excessive phlegm (mucus), been taking any medications, an allergy to plants of the Geraniaceae family.

Stop Use

Stop use and ask a doctor if new symptoms occur, symptoms get worse or last more than 7 days, fever worsens or lasts more than 3 days, or cough lasts more than 7 days or occurs with rash or persistent headache.

These could be signs of a serious condition.

Pregnancy or Breast Feeding

If pregnant or breast-feeding, ask a healthcare professional before use.

Keep out of reach of children

Overdose

In case of overdose, seeek medical help or contact a Poison Control Center right away.